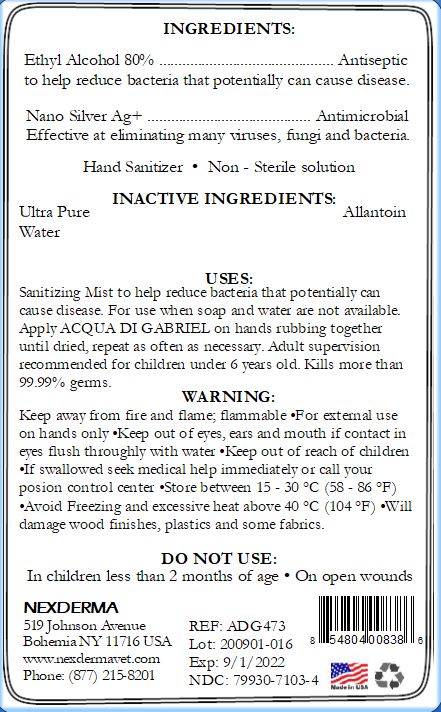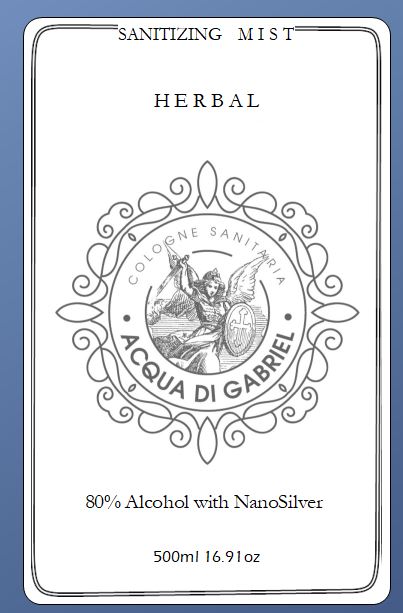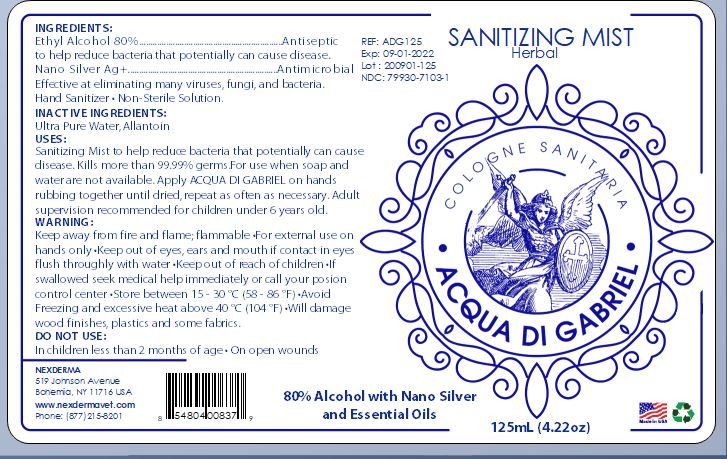 DRUG LABEL: Acqua Di Gabriel
NDC: 79930-7103 | Form: SPRAY
Manufacturer: Nexderma Inc
Category: otc | Type: HUMAN OTC DRUG LABEL
Date: 20200903

ACTIVE INGREDIENTS: ALCOHOL 80 mL/100 mL
INACTIVE INGREDIENTS: ALLANTOIN 0.03 mL/100 mL; WATER 20 mL/100 mL; SILVER 0.5 mL/100 mL

ACTIVE INGREDIENT

Ethyl Alcohol 80%- Antiseptic to help reduce bacteria that potentially can cause disease

INACTIVE INGREDIENT

Allantoin

Ultra Pure Water

Silver

INDICATIONS AND USAGE

Hand Sanitizer to help reduce bacteria that potentially can cause disease. For use when soap and water are not available. Apply Defense Ag on hands rubbing together until dried. Repeat as often as necessary.

KEEP OUT OF REACH OF CHILDREN

Adult supervision recommended for children under 6 years old.

WARNINGS

Keep away form fire and flame.

Flammable

For external use on hands only.

Keep out of eye, ears and mouth.

If contact in eyes, flush thoroughly with water.

Keep out of reach of children.

If swallowed seek medical help immediately or call your poison control center.

Store between 15-30 (58-86F)

Avoid freezing and excessive heat above 40C (104F)

Will damage wood finishes, plastics and some fabrics.

DO NOT USE

Children less than 2 months of age or on open wounds.

Dosage: upto 10 times a day

Place enough product on hands to cover all surfaces. Rub hands together until dry.

Administration:Topoical

PURPOSE

Purpose: to help reduce bacteria that potentially can cause disease. For use when soap and water are not available.